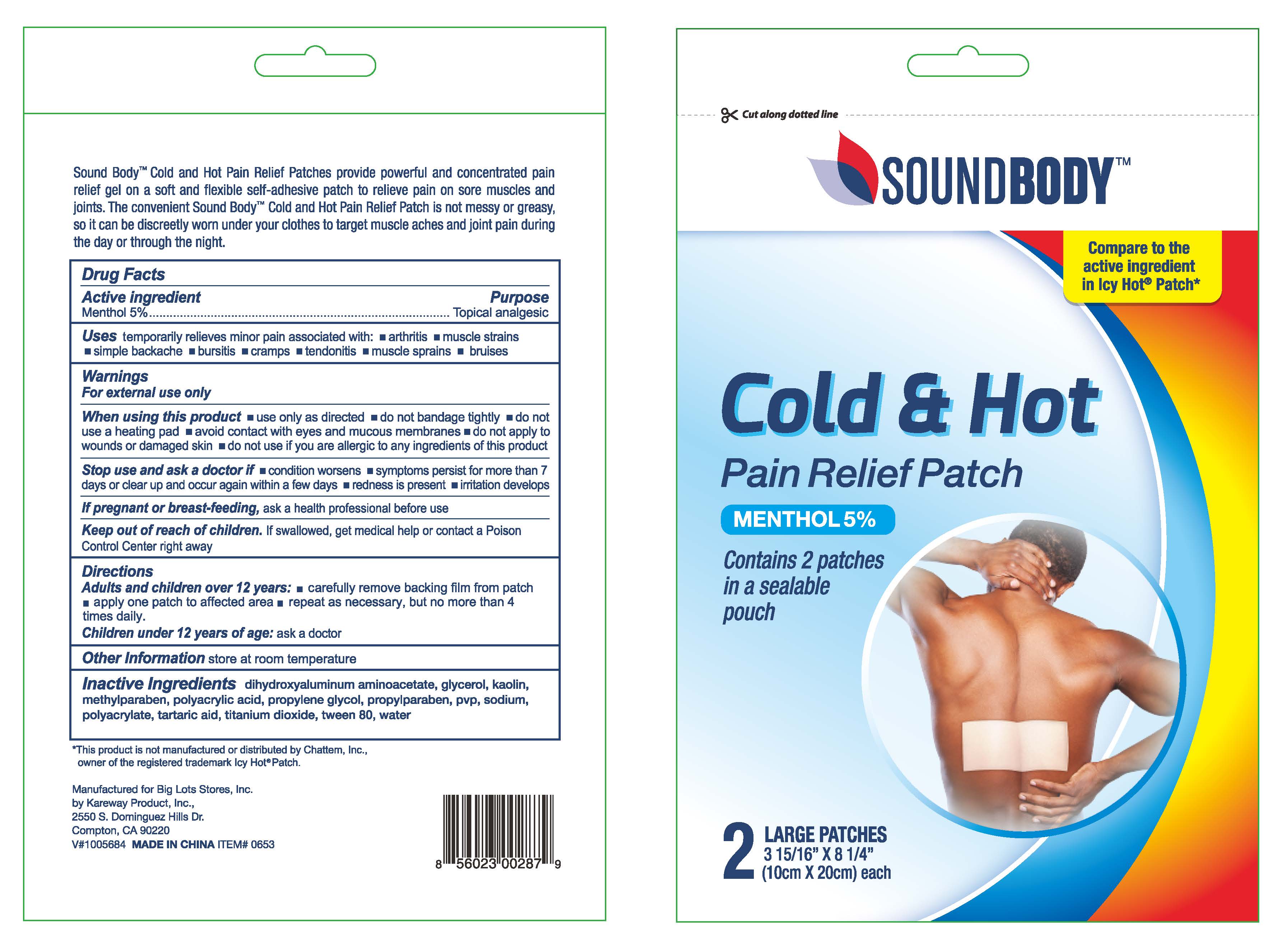 DRUG LABEL: Soundbody Cold and Hot Pain Relief
NDC: 67510-0287 | Form: PATCH
Manufacturer: Kareway Product, Inc.
Category: otc | Type: HUMAN OTC DRUG LABEL
Date: 20220321

ACTIVE INGREDIENTS: MENTHOL 400 mg/1 1
INACTIVE INGREDIENTS: POLYACRYLIC ACID (8000 MW); POLYSORBATE 80; SODIUM POLYACRYLATE (8000 MW); GLYCERIN; DIHYDROXYALUMINUM AMINOACETATE; KAOLIN; METHYLPARABEN; PROPYLENE GLYCOL; PROPYLPARABEN; WATER; TARTARIC ACID; TITANIUM DIOXIDE; POVIDONE; MINERAL OIL; PETROLATUM

Soundbody Cold and Hot Pain Relief

Active Ingredient

Menthol 5%

Purpose

Topical analgesic

Uses

Temporarily relieves minor pain associated with:

- arthritis
- muscle strains
- simple backache
- bursitis
- cramps
- tendonitis
- muscle sprains
- bruises

Warnings

For external use only

When using this product

- use only as directed
- do not bandage tightly
- do not use a heating pad
- avoid contact with eyes and mucous membrane
- do not apply to wounds or damaged skin
- do not use if you are allergic to any ingredients of this product

Stop use and ask a doctor if

- condition worsens
- symptoms persist for more than 7 days or clear up and occur again within a few days
- redness is present
- irritation develops

If pregnant or breast-feeding,

ask a health professional before use.

Keep out of reach of children.

If swallowed, get medical help or contact a Poison Control Center right away.

Directions

Adults and children over 12 years:

- Remove backing from patch by grasping both ends firmly and gently pulling until backing separates in middle
- Carefully remove backing from patch
- Apply one patch to affected area
- Repeat as necessary, but no more than 4 times daily

Children under 12 years of age: Ask a doctor

Other information

store at room temperature

Inactive ingredients

dihydroxyaluminum aminoacetate, glycerol, kaolin, methylparaben, polyacrylic acid, propylene glycol, propylparaben, pvp, sodium polyacrylate, tartaric acid, titanium dioxide, tween 80, water

package label

Cold and Hot Pain Relief Patch